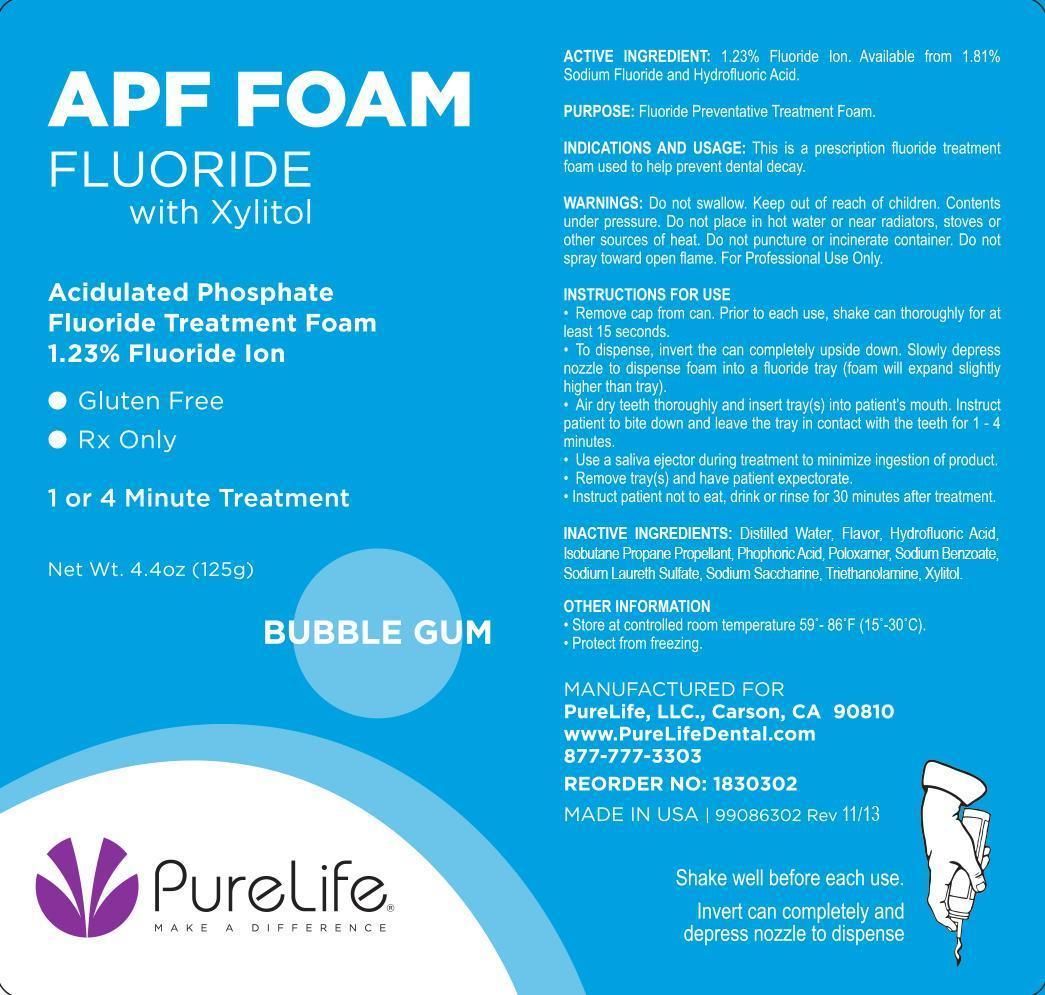 DRUG LABEL: PureLife APF
NDC: 68987-024 | Form: AEROSOL, FOAM
Manufacturer: PureLife Dental
Category: prescription | Type: HUMAN PRESCRIPTION DRUG LABEL
Date: 20140514

ACTIVE INGREDIENTS: SODIUM FLUORIDE 1.5375 g/125 g
INACTIVE INGREDIENTS: Water; HYDROFLUORIC ACID; PHOSPHORIC ACID; POLOXAMER 407; SODIUM BENZOATE; SODIUM LAURETH-3 SULFATE; SACCHARIN SODIUM; TROLAMINE; XYLITOL

Active Ingredient:

1.23% Fluoride Ion.

Available from 1.81% Sodium Fluoride and Hydrofluoric Acid.

Purpose:

Fluoride Preventative Treatment Foam.

Indications and Usage:

This is a prescription fluoride treatment foam used to help prevent dental decay.

Warnings:

Do not swallow. Keep out of reach of children. Contents under pressure. Do not place in hot water or near radiators, stoves, or other sources of heat. Do not puncture or incinerate container. Do not spray toward open flame. For Professional Use Only.

Instructions for Use

- Remove cap from can. Prior to each use, shake can thoroughly for at least 15 seconds.
- To dispense, invert the can completely upside down. Slowly depress nozzle to dispense foam into fluoride tray (foam will expand slightly higher than the tray).
- Air dry teeth thoroughly and insert tray(s) into patient's mouth. Instruct patient to bite down and leave the tray in contact with the teeth for 1-4 minutes.
- Use a saliva ejector during treatment to minimize ingestion of the product.
- Remove tray(s) and have patient expectorate.
- Instruct patient not to eat, drink or rinse for 30 minutes after treatment.

Inactive Ingredients

Distilled Water, Flavor, Hydrofluoric Acid, Isobutane Propane Propellant, Phosphoric Acid, Poloxamer, Sodium Benzoate, Sodium Laureth Sulfate, Sodium Saccharin, Triethanolamine, Xylitol.

Other Information:

Store at controlled room temperature 59°-86°F (15°-30°C).

Protect from freezing.